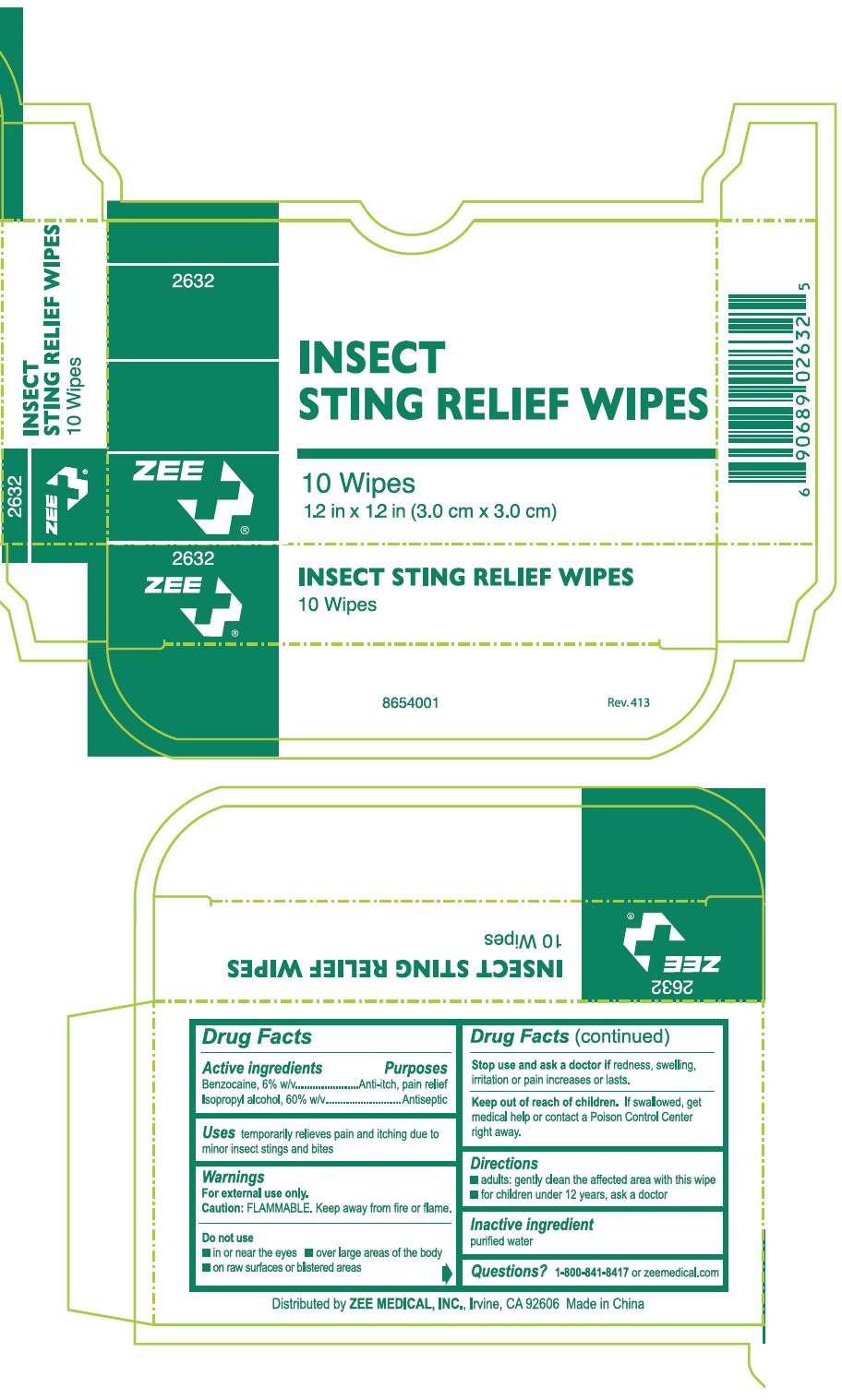 DRUG LABEL: Insect Sting Relief Wipes
NDC: 35418-263 | Form: SWAB
Manufacturer: ZEE MEDICAL
Category: otc | Type: HUMAN OTC DRUG LABEL
Date: 20130605

ACTIVE INGREDIENTS: BENZOCAINE 60 mg/1 mL; ISOPROPYL ALCOHOL 0.60 mL/1 mL
INACTIVE INGREDIENTS: Water

ZEE Insect Sting Relief Wipes

ZEE Insect Sting Relief Wipes

Drug Facts

ACTIVE INGREDIENT

PURPOSE

Active ingredients | Purposes
Benzocaine, 6% w/v | Anti-itch, pain relief
Isopropyl alcohol, 60% w/v | Antiseptic

Uses

temporarily relieves pain and itching due to minor insect stings and bites

Warnings

For external use only.

Caution: FLAMMABLE. Keep away from fire or flame.

Do not use

- in or near the eyes
- over large areas of the body
- on raw surfaces or blistered areas

Stop use and ask a doctor if redness, swelling, irritation or pain increases or lasts.

Keep out of reach of children. If swallowed, get medical help or contact a Poison Control Center right away.

Directions

- adults: gently clean the affected area with this wipe
- for children under 12 years, ask a doctor

Inactive ingredient

purified water

Questions?

1-800-841-8417 or zeemedical.com

Distributed by ZEE MEDICAL, INC., Irvine, CA 92606

ZEE Insect Sting Relief Wipes

2632

INSECT
STING RELIEF WIPES

ZEE+

10 Wipes
1.2 in x 1.2 in (3.0 cm x 3.0 cm)